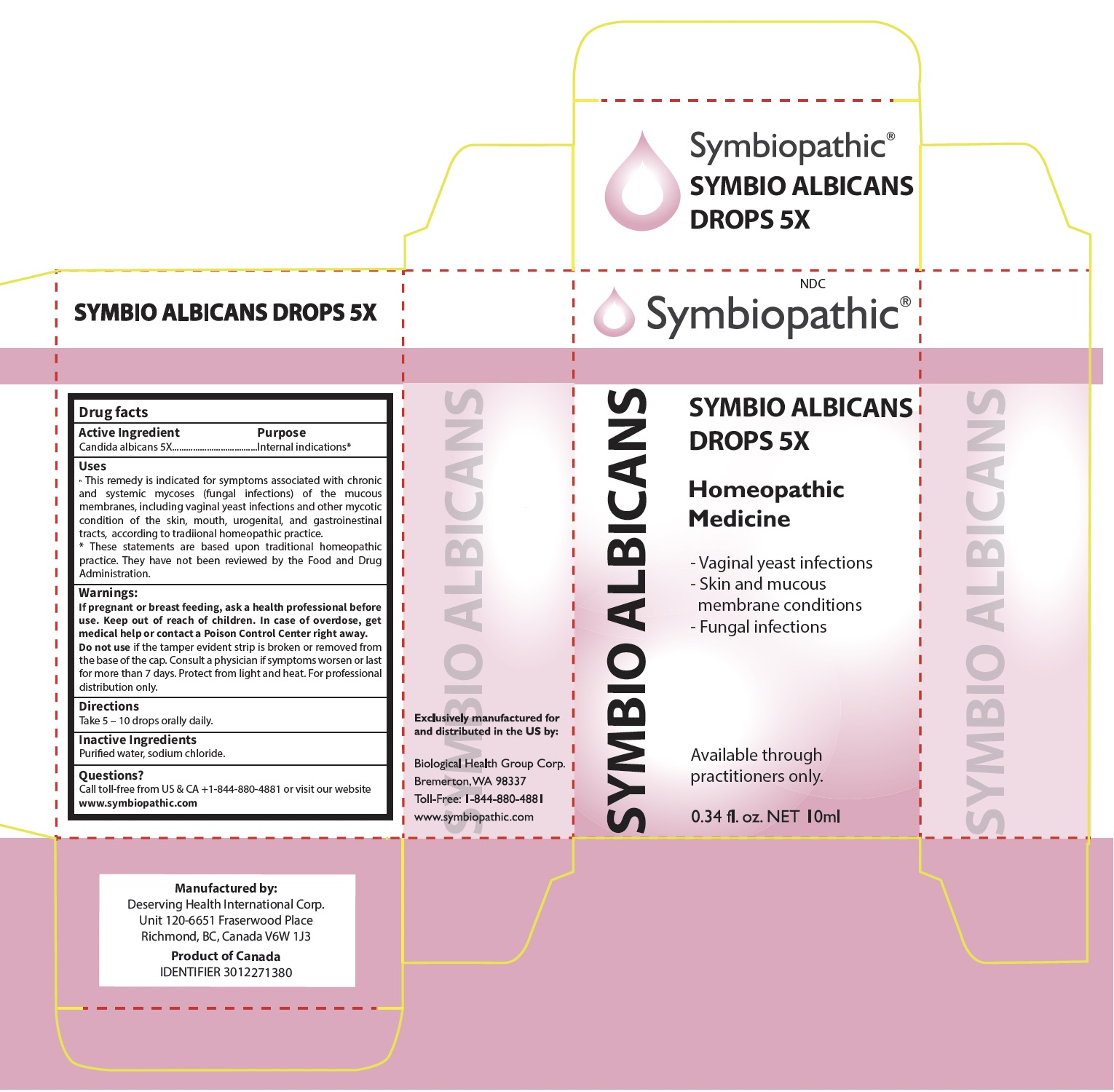 DRUG LABEL: SYMBIO ALBICANS DROPS
NDC: 69710-195 | Form: LIQUID
Manufacturer: Symbiopathic
Category: homeopathic | Type: HUMAN OTC DRUG LABEL
Date: 20251217

ACTIVE INGREDIENTS: CANDIDA ALBICANS 5 [hp_X]/1 mL
INACTIVE INGREDIENTS: SODIUM CHLORIDE; WATER

ALBICANS 5 X

ACTIVE INGREDIENTS:

Candida Albicans 5X

INDICATIONS:

This remedy is indicated for symptoms associated with yeast infections and intestinal dysbacteria according to traditional homeopathic practice.*

PURPOSE:

For internal indications

WARNINGS:

If pregnant or breast feeding, ask a health professional before use. Keep out of reach of children. In case of overdose, get medical help or contact a Poison Control Center right away.

Do not use if the tamper evident strip is broken or removed from the base of the cap. Consult a physician if symptoms worsen or last for more than 7 days. Protect from light and heat. For professional distribution

DIRECTIONS:

Take 5 – 10 drops orally, three times per day.

INACTIVE INGREDIENTS:

Purified water USP, sodium chloride

KEEP OUT OF REACH OF CHILDREN:In case of overdose, get medical help or call a Poison Control Center right away.

QUESTIONS:

Call toll-free from US & CA +1-844-880-4881 or visit our website
www.biological-health.com

OTHER INFORMATION:

Protect from light and heat.

For professional distribution only.

*These statements are based upon traditional homeopathic practice. They have not been reviewed by the Food and Drug Administration.